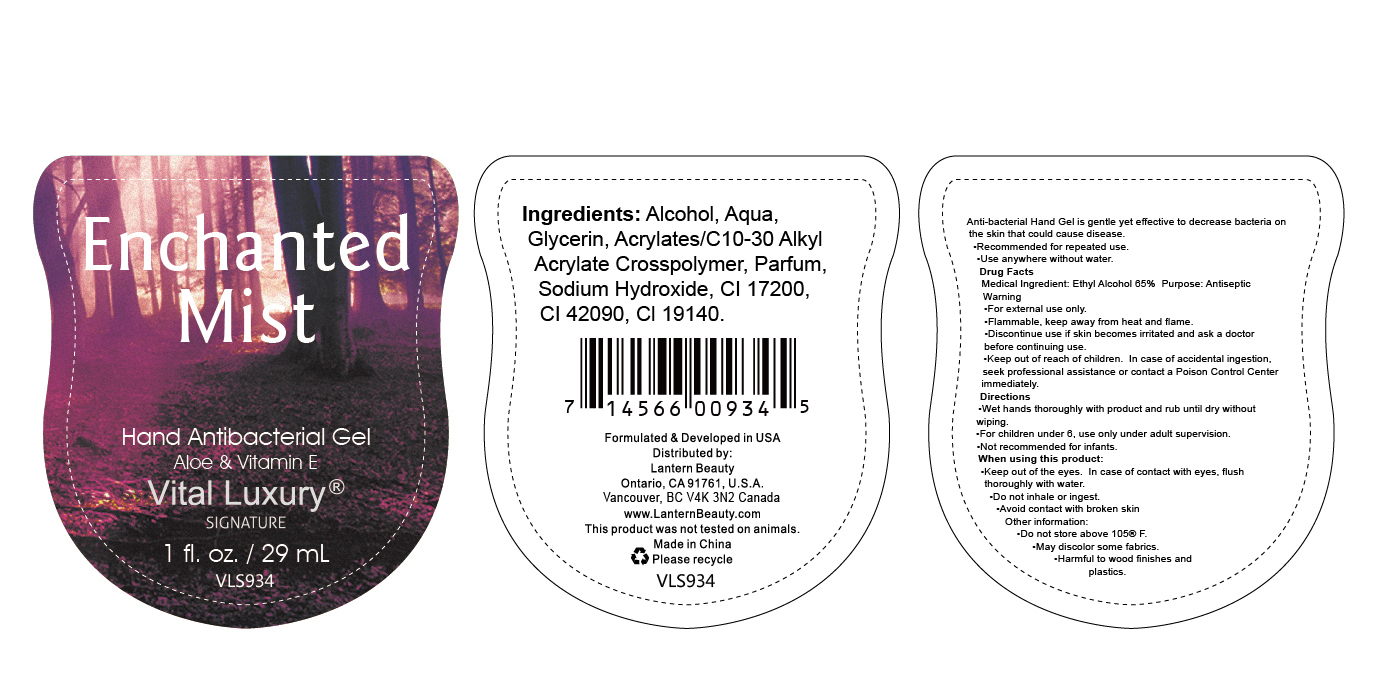 DRUG LABEL: Hand sanitizer 29ml
NDC: 54860-405 | Form: GEL
Manufacturer: Shenzhen Lantern Scicence Co.,Ltd.
Category: otc | Type: HUMAN OTC DRUG LABEL
Date: 20250205

ACTIVE INGREDIENTS: ALCOHOL 65 mL/100 mL
INACTIVE INGREDIENTS: SODIUM HYDROXIDE; GLYCERIN; ACRYLATES/C10-30 ALKYL ACRYLATE CROSSPOLYMER (60000 MPA.S); WATER; FD&C YELLOW NO. 5; FD&C BLUE NO. 1; D&C RED NO. 33

Hand sanitizer 29ml

Drug Facts

Medical Ingredient

Ethyl Alcohol 65% purpose：Antiseptic

keep out of reach of children

In case of accidental ingestion.
seek professional assistance or contact a Poison Control Center immediately.

DOSAGE AND ADMINISTRATION

Recommended for repeated use.

use anywhere without water.

Warning

For external use only.

Flammable,Keep away from heat or flame.

Discontinue use if skin becomes irritated and ask a doctor before continuing use.

WARNINGS AND PRECAUTIONS

For external use only.

Flammable, keep away from heat and flame.

STOP USE

Discontinue if skin becomes irritated and ask a doctor .

Keep out of reach of children. In case of accidental ingestion, seek professional assistance or contact a poson control center immediately.

Inactive ingredients

Aqua, Glycerin, Acrylates/C10-30 Alkyl Acrylate Crosspolymer, Parfum, sodium hydroxide,CI 17200,CI 42090,CI 19140.

Directions

Wet hands thoroughly with product and rub until dry without wiping.

When using this product

keep out of eyes. In case of contact with eyes, flush thoroughly with water.

Do not inhale or ingest.

Avoid contact with broken skin.

Other information

Do not store above 105F.

May discolor some fabrics.

Harmful to wood finishes and plastics.

When using this product

Keep out of the eyes. In case of contact with eyes. flush thoroughly with water.
Do not inhale or ingest.
Avoid contact with broken skin

Purpose

Antiseptic

Stop use and ask a doctor

if irritation or rash occurs,these may be signs of a serious condition.

Use

Anti-bacterial Hand Gel is gentle yet effective to decrease bacteria on the skin that could cause disease.
Recommended for repeated use.
Use anywhere without water.

Other information

Do not store above 105 F.
May discolor some fabrics.
Harmful to wood finishes and plastics.

Do not use

in children less than 2 months of age

on open skin wounds.

Packaging